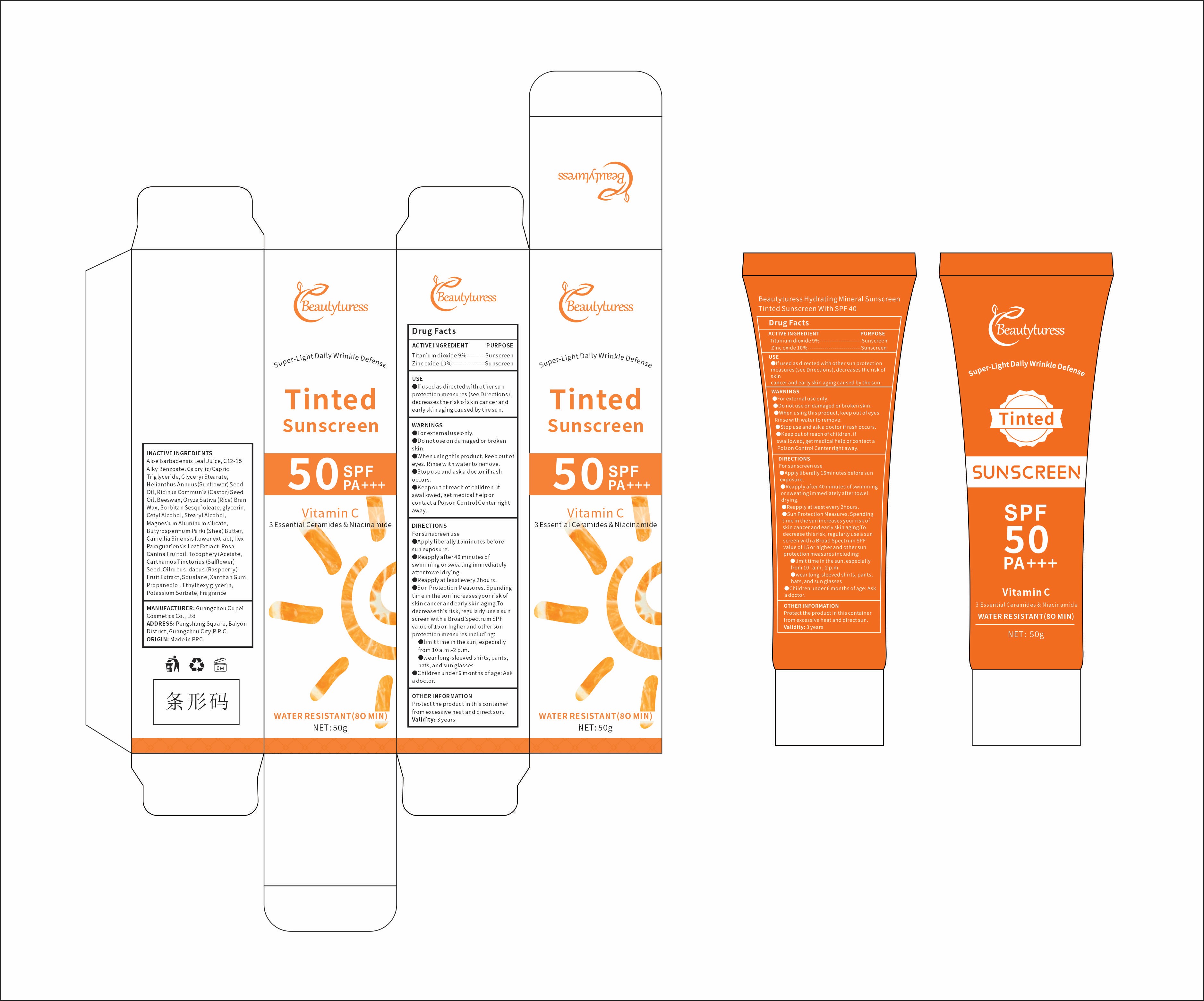 DRUG LABEL: Beautyturess Tinted Sunscreen
NDC: 84753-001 | Form: EMULSION
Manufacturer: Guangdong Bisutang Biotechnology Co., Ltd.
Category: otc | Type: HUMAN OTC DRUG LABEL
Date: 20240928

ACTIVE INGREDIENTS: ZINC OXIDE 50 mg/50 mg; TITANIUM DIOXIDE 50 mg/50 mg
INACTIVE INGREDIENTS: SORBITAN SESQUIOLEATE; CASTOR OIL; POTASSIUM SORBATE; GLYCERYL MONOSTEARATE; GLYCERIN; ALKYL (C12-15) BENZOATE; MAGNESIUM ALUMINUM SILICATE; SHEA BUTTER; ETHYLHEXYLGLYCERIN; XANTHAN GUM; SUNFLOWER OIL; YELLOW WAX; RICE BRAN; SAFFLOWER SEED; ALOE VERA LEAF; ROSA CANINA FRUIT OIL; CETYL ALCOHOL; ILEX PARAGUARIENSIS LEAF; BRASSICA NAPUS SUBSP. NAPUS SEED; SQUALANE; STEARYL ALCOHOL; MEDIUM-CHAIN TRIGLYCERIDES; CAMELLIA SINENSIS FLOWER; .GAMMA.-TOCOPHEROL, DL-; PROPANEDIOL; MYRISTICA FRAGRANS WHOLE

Active Ingredient

Titanium dioxide 9%
Zinc oxide 10%

PURPOSE

Helps prevent sunburn
If used as directed with other sun protection measures (see Directions), decreases the risk of skin cancer and early skin aging caused by the sun

Ask Doctor

Children under 6 months of age:

Directions

Apply liberally/generously (and evenly) 15 minutes before sun exposure
For use on children less than 6 months of age, consult a health care practitioner
Reapply
At least every 2 hours
After 80 minutes of swimming or sweating
Immediately after towel drying
after eating or drinking

Mode d'emploi

Appliquer généreusement (et uniformément) 15 minutes avant l'exposition au soleil
Pour les enfants agés de moins de 6 mois, consulter un praticien de soins de santé
Appliquer denouveau:
au moins toutes les 2 heures
aprés 80 minutes de baignade ou aprés avoir mangé ou bu.

WHEN USING

If used as directed with other sun protection measures (see Directions), decreases the risk of skin cancer and early skin aging caused by the sun.

WARNINGS

Risk InformationFor external use only
Mention de risquesPour usage externe seulement
Do not use on damaged or broken skin.
Ne pas utiliser sur la peau endommagée ou avec des lésions
If rash occurs, discontinue use and consult a health care practitioner.
En présence d'une éruption cutanée, cesser l'utilisation et consulter un praticien de soins de santé
When using this product keep out of eyes. Rinse with water to remove.
Eviter tout contact avec les yeux. Rincer a l'eau le cas échéant
Keep out of reach of children. If swallowed, get medical help or contact a Poison Control Center right away.
Tenir hors de portée des enfants
En cas d'ingestion, consulter un médecin ou appeler un centre antipoison immédiatement.

INDICATIONS AND USAGE

Sun Protection Measures Spending time in the sun increases your risk of skin cancer and early skin aging. To decrease this risk, regularly use a sunscreen with a broad spectrum SPF value of 15 or higher and other sun protection measures including

Limit time in the sun, especially from 10 a.m.-2 p.m.
Wear long-sleeved shirts, pants, hats, and sun glasses.

Mesures de protection contre le soleil Passer du temps au soleil augmente le risque de cancer de la peau et de vieillissement prématuré de la peau. Afin de diminuer ce risque, il convient d'utiliser réeguliérement un écran solaire avec un F.P.S. a large spectre d'au moins 15 et d'appliquer d'autres mesures de protection contre le soleil, telles que

limiter le temps passé au soleil notamment entre 10 et 14 heures
porter des chemises a manches longues, des pantalons, un chapeau et des lunettes de soleil.

Keep out of reach of children. If swallowed, get medical help or contact a Poison Control Center right away.
Tenir hors de portée des enfants
En cas d'ingestion, consulter un médecin ou appeler un centre antipoison immédiatement.

INACTIVE INGREDIENT

Aloe Barbadensis Leaf Juice, C12-15 Alky Benzoate, Caprylic/Capric Triglyceride, Glyceryi Stearate, Helianthus Annuus(Sunflower) Seed Oil, Ricinus Communis (Castor) Seed Oil, Beeswax, Oryza Sativa (Rice) Bran Wax, Sorbitan Sesquioleate，glycerin, Cetyi Alcohol, Stearyl Alcohol, Magnesium Aluminum silicate, Butyrospermum Parki (Shea) Butter, Camellia Sinensis flower extract, Ilex Paraguariensis Leaf Extract, Rosa Canina Fruitoil, Tocopheryi Acetate, Carthamus Tinctorius (Safflower) Seed, Oilrubus Idaeus (Raspberry) Fruit Extract, Squalane, Xanthan Gum, Propanediol, Ethylhexy glycerin, Potassium Sorbate, Fragrance